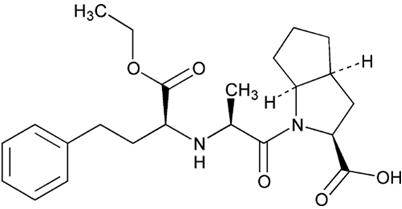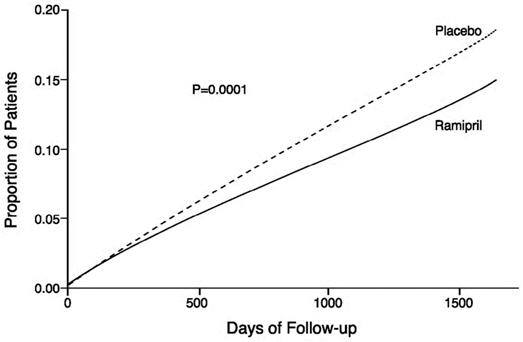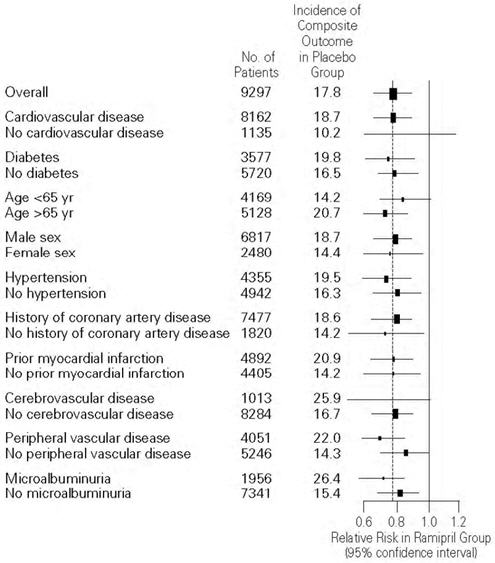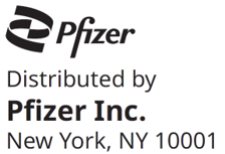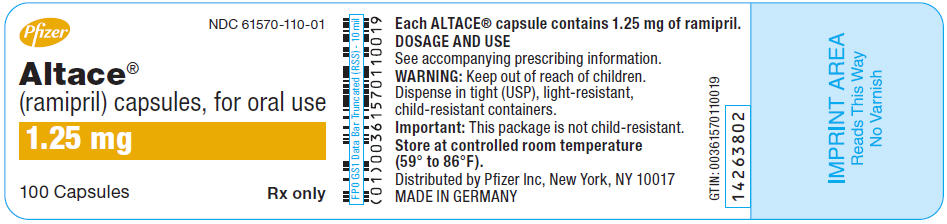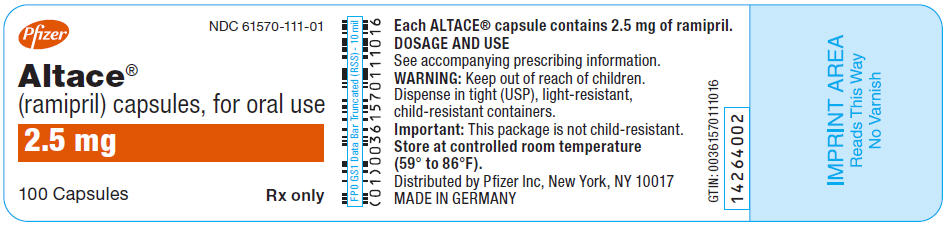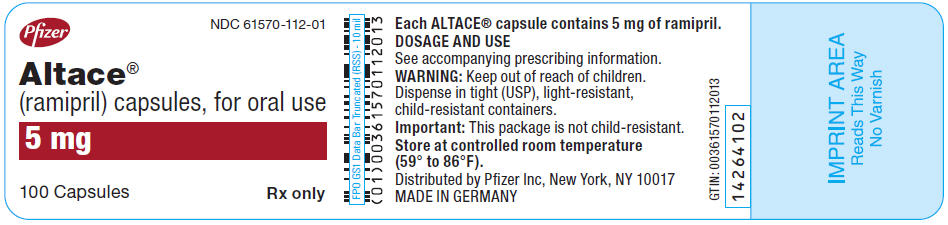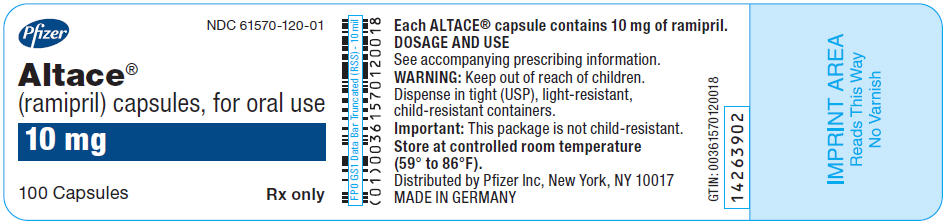 DRUG LABEL: ALTACE
NDC: 61570-110 | Form: CAPSULE
Manufacturer: Pfizer Laboratories Div Pfizer Inc
Category: prescription | Type: HUMAN PRESCRIPTION DRUG LABEL
Date: 20250708

ACTIVE INGREDIENTS: RAMIPRIL 1.25 mg/1 1
INACTIVE INGREDIENTS: STARCH, CORN; GELATIN, UNSPECIFIED; TITANIUM DIOXIDE; FERRIC OXIDE YELLOW

HIGHLIGHTS OF PRESCRIBING INFORMATION

These highlights do not include all the information needed to use ALTACE safely and effectively. See full prescribing information for ALTACE.
ALTACE® (ramipril) capsules, for oral use
Initial U.S. Approval: 1991

WARNING: FETAL TOXICITY

See full prescribing information for complete boxed warning

- When pregnancy is detected, discontinue ALTACE as soon as possible (5.6).
- Drugs that act directly on the renin-angiotensin system can cause injury and death to the developing fetus (5.6).

RECENT MAJOR CHANGES

Contraindications (4) | 04/2017
Warnings and Precautions, Anaphylactoid and Possibly Related Reactions (5.1) | 04/2017

1 INDICATIONS AND USAGE

ALTACE is an angiotensin converting enzyme (ACE) inhibitor indicated for the treatment of hypertension, to lower blood pressure. Lowering blood pressure reduces the risk of fatal and nonfatal cardiovascular events, primarily strokes and myocardial infarctions. It may be used alone or in combination with thiazide diuretics (1.1).

In patients 55 years or older at high risk of developing a major cardiovascular event, ALTACE is indicated to reduce the risk of myocardial infarction, stroke, or death from cardiovascular causes (1.2).

ALTACE is indicated in stable patients who have demonstrated clinical signs of congestive heart failure post-myocardial infarction (1.3).

2 DOSAGE AND ADMINISTRATION

Hypertension: Initial dose is 2.5 mg to 20 mg once daily. Adjust dosage according to blood pressure response after 2–4 weeks of treatment. The usual maintenance dose following titration is 2.5 mg to 20 mg daily as a single dose or equally divided doses (2.1).

Reduction in the risk of myocardial infarction, stroke, or death from cardiovascular causes: 2.5 mg once daily for 1 week, 5 mg once daily for 3 weeks, and increased as tolerated to a maintenance dose of 10 mg once daily (2.2).

Heart failure post-myocardial infarction: Starting dose of 2.5 mg twice daily. If patient becomes hypotensive at this dose, decrease dosage to 1.25 mg twice daily. Increase dose as tolerated toward a target dose of 5 mg twice daily, with dosage increases about 3 weeks apart (2.3).

Dosage adjustment: See respective sections pertaining to dosage adjustment in special situations (2.5).

3 DOSAGE FORMS AND STRENGTHS

Capsule: 1.25 mg, 2.5 mg, 5 mg, 10 mg (3)

4 CONTRAINDICATIONS

Angioedema related to previous treatment with an ACE inhibitor, or a history of hereditary or idiopathic angioedema (4).

ALTACE is contraindicated in combination with a neprilysin inhibitor (e.g., sacubitril). Do not administer ALTACE within 36 hours of switching to or from sacubitril/valsartan, a neprilysin inhibitor (4).

Do not co-administer aliskiren with ALTACE in patients with diabetes (4).

5 WARNINGS AND PRECAUTIONS

Angioedema, increased risk in patients with a prior history (5.1)

Hypotension and hyperkalemia (5.5, 5.8)

Renal impairment: monitor renal function during therapy (5.3)

Avoid concomitant use of an ACE inhibitor and angiotensin blocker (5.7)

Rare cholestatic jaundice and hepatic failure (5.2)

Rare neutropenia and agranulocytosis (5.4)

6 ADVERSE REACTIONS

The most common adverse reactions in patients with hypertension included headache, dizziness, fatigue, and cough (6.1).

To report SUSPECTED ADVERSE REACTIONS, contact Pfizer at 1-800-438-1985 or the FDA at 1-800-FDA-1088 or www.fda.gov/medwatch.

7 DRUG INTERACTIONS

Diuretics: Possibility of excessive hypotension (7.1).

Lithium: Use with caution (7.4).

Gold: Nitritoid reactions have been reported (7.5).

NSAIDS use may lead to increased risk of renal impairment and loss of antihypertensive effect (7.6).

mTOR inhibitor or neprilysin inhibitor use may increase angioedema risk (7.7).

8 USE IN SPECIFIC POPULATIONS

Pregnancy: Discontinue drug if pregnancy is detected (5.6, 8.1).

Nursing mothers: ALTACE use is not recommended in nursing mothers (8.3).

FULL PRESCRIBING INFORMATION

WARNING: FETAL TOXICITY

- When pregnancy is detected, discontinue ALTACE as soon as possible (5.6).
- Drugs that act directly on the renin-angiotensin system can cause injury and death to the developing fetus (5.6).

1 INDICATIONS AND USAGE

1.1 Hypertension

ALTACE is indicated for the treatment of hypertension, to lower blood pressure. Lowering blood pressure reduces the risk of fatal and nonfatal cardiovascular events, primarily strokes and myocardial infarctions. These benefits have been seen in controlled trials of antihypertensive drugs from a wide variety of pharmacologic classes including this drug.

Control of high blood pressure should be part of comprehensive cardiovascular risk management, including, as appropriate, lipid control, diabetes management, antithrombotic therapy, smoking cessation, exercise, and limited sodium intake. Many patients will require more than one drug to achieve blood pressure goals. For specific advice on goals and management, see published guidelines, such as those of the National High Blood Pressure Education Program's Joint National Committee on Prevention, Detection, Evaluation, and Treatment of High Blood Pressure (JNC).

Numerous antihypertensive drugs, from a variety of pharmacologic classes and with different mechanisms of action, have been shown in randomized controlled trials to reduce cardiovascular morbidity and mortality, and it can be concluded that it is blood pressure reduction, and not some other pharmacologic property of the drugs, that is largely responsible for those benefits. The largest and most consistent cardiovascular outcome benefit has been a reduction in the risk of stroke, but reductions in myocardial infarction and cardiovascular mortality also have been seen regularly.

Elevated systolic or diastolic pressure causes increased cardiovascular risk, and the absolute risk increase per mmHg is greater at higher blood pressures, so that even modest reductions of severe hypertension can provide substantial benefit. Relative risk reduction from blood pressure reduction is similar across populations with varying absolute risk, so the absolute benefit is greater in patients who are at higher risk independent of their hypertension (for example, patients with diabetes or hyperlipidemia), and such patients would be expected to benefit from more aggressive treatment to a lower blood pressure goal.

Some antihypertensive drugs have smaller blood pressure effects (as monotherapy) in black patients, and many antihypertensive drugs have additional approved indications and effects (e.g., on angina, heart failure, or diabetic kidney disease). These considerations may guide selection of therapy.

ALTACE may be used alone or in combination with thiazide diuretics.

1.2 Reduction in the Risk of Myocardial Infarction, Stroke, and Death from Cardiovascular Causes

ALTACE is indicated in patients 55 years or older at high risk of developing a major cardiovascular event because of a history of coronary artery disease, stroke, peripheral vascular disease, or diabetes that is accompanied by at least one other cardiovascular risk factor (hypertension, elevated total cholesterol levels, low HDL levels, cigarette smoking, or documented microalbuminuria), to reduce the risk of myocardial infarction, stroke, or death from cardiovascular causes. ALTACE can be used in addition to other needed treatment (such as antihypertensive, antiplatelet, or lipid-lowering therapy) [see Clinical Studies (14.2)].

1.3 Heart Failure Post-Myocardial Infarction

ALTACE is indicated in stable patients who have demonstrated clinical signs of congestive heart failure within the first few days after sustaining acute myocardial infarction. Administration of ALTACE to such patients has been shown to decrease the risk of death (principally cardiovascular death) and to decrease the risks of failure-related hospitalization and progression to severe/resistant heart failure [see Clinical Studies (14.3)].

2 DOSAGE AND ADMINISTRATION

2.1 Hypertension

The recommended initial dose for patients not receiving a diuretic is 2.5 mg once a day. Adjust dose according to blood pressure response. The usual maintenance dosage range is 2.5 mg to 20 mg per day administered as a single dose or in two equally divided doses. In some patients treated once daily, the antihypertensive effect may diminish toward the end of the dosing interval. In such patients, consider an increase in dosage or twice daily administration. If blood pressure is not controlled with ALTACE alone, a diuretic can be added.

2.2 Reduction in Risk of Myocardial Infarction, Stroke, and Death from Cardiovascular Causes

Initiate dosing at 2.5 mg once daily for 1 week, 5 mg once daily for the next 3 weeks, and then increase as tolerated, to a maintenance dose of 10 mg once daily. If the patient is hypertensive or recently post-myocardial infarction, ALTACE can also be given as a divided dose.

2.3 Heart Failure Post-Myocardial Infarction

For the treatment of post-myocardial infarction patients who have shown signs of congestive heart failure, the recommended starting dose of ALTACE is 2.5 mg twice daily (5 mg per day). A patient who becomes hypotensive at this dose may be switched to 1.25 mg twice daily. After one week at the starting dose, increase dose (if tolerated) toward a target dose of 5 mg twice daily, with dosage increases being about 3 weeks apart.

After the initial dose of ALTACE, observe the patient under medical supervision for at least two hours and until blood pressure has stabilized for at least an additional hour. If possible, reduce the dose of any concomitant diuretic as this may diminish the likelihood of hypotension. The appearance of hypotension after the initial dose of ALTACE does not preclude subsequent careful dose titration with the drug, following effective management of the hypotension [see Warnings and Precautions (5.5), Drug Interactions (7.1)].

2.4 General Dosing Information

Generally, swallow ALTACE capsules whole. The ALTACE capsule can also be opened and the contents sprinkled on a small amount (about 4 oz.) of applesauce or mixed in 4 oz. (120 mL) of water or apple juice. To be sure that ramipril is not lost when such a mixture is used, consume the mixture in its entirety. The described mixtures can be pre-prepared and stored for up to 24 hours at room temperature or up to 48 hours under refrigeration.

Concomitant administration of ALTACE with potassium supplements, potassium salt substitutes, or potassium-sparing diuretics can lead to increases of serum potassium [see Warnings and Precautions (5.8)].

2.5 Dosage Adjustment

Renal Impairment

Establish baseline renal function in patients initiating ALTACE. Usual regimens of therapy with ALTACE may be followed in patients with estimated creatinine clearance >40 mL/min. However, in patients with worse impairment, 25% of the usual dose of ramipril is expected to produce full therapeutic levels of ramiprilat [see Use in Specific Populations (8.6)].

Hypertension

For patients with hypertension and renal impairment, the recommended initial dose is 1.25 mg ALTACE once daily. Dosage may be titrated upward until blood pressure is controlled or to a maximum total daily dose of 5 mg.

Heart Failure Post-Myocardial Infarction

For patients with heart failure and renal impairment, the recommended initial dose is 1.25 mg ALTACE once daily. The dose may be increased to 1.25 mg twice daily, and up to a maximum dose of 2.5 mg twice daily depending on clinical response and tolerability.

Volume Depletion or Renal Artery Stenosis

Blood pressure decreases associated with any dose of ALTACE depend, in part, on the presence or absence of volume depletion (e.g., past and current diuretic use) or the presence or absence of renal artery stenosis. If such circumstances are suspected to be present, initiate dosing at 1.25 mg once daily. Adjust dosage according to blood pressure response.

3 DOSAGE FORMS AND STRENGTHS

ALTACE (ramipril) is supplied as hard gelatin capsules containing 1.25 mg, 2.5 mg, 5 mg, and 10 mg of ramipril.

4 CONTRAINDICATIONS

ALTACE is contraindicated in patients who are hypersensitive to this product or any other ACE inhibitor (e.g., a patient who has experienced angioedema during therapy with any other ACE inhibitor).

ALTACE is contraindicated in combination with a neprilysin inhibitor (e.g., sacubitril). Do not administer ALTACE within 36 hours of switching to or from sacubitril/valsartan, a neprilysin inhibitor [see Warnings and Precautions (5.1)].

Do not co-administer ALTACE with aliskiren:

- in patients with diabetes

5 WARNINGS AND PRECAUTIONS

5.1 Anaphylactoid and Possibly Related Reactions

Presumably because drugs that act directly on the renin-angiotensin-aldosterone system (e.g., ACE inhibitors) affect the metabolism of eicosanoids and polypeptides, including endogenous bradykinin, patients receiving these drugs (including ALTACE) may be subject to a variety of adverse reactions, some of them serious.

Angioedema

Head and Neck Angioedema

Patients with a history of angioedema unrelated to ACE inhibitor therapy may be at increased risk of angioedema while receiving an ACE inhibitor.

Angioedema of the face, extremities, lips, tongue, glottis, and larynx has been reported in patients treated with ACE inhibitors. Angioedema associated with laryngeal edema can be fatal. If laryngeal stridor or angioedema of the face, tongue, or glottis occurs, discontinue treatment with ALTACE and institute appropriate therapy immediately. Where there is involvement of the tongue, glottis, or larynx likely to cause airway obstruction, administer appropriate therapy (e.g., subcutaneous epinephrine solution 1:1000 [0.3 mL to 0.5 mL]) promptly [see Adverse Reactions (6)].

In considering the use of ALTACE, note that in controlled clinical trials ACE inhibitors cause a higher rate of angioedema in Black patients than in non-Black patients.

In a large U.S. post-marketing study, angioedema (defined as reports of angio, face, larynx, tongue, or throat edema) was reported in 3/1523 (0.20%) Black patients and in 8/8680 (0.09%) non-Black patients. These rates were not different statistically.

Patients taking concomitant mammalian target of rapamycin (mTOR) inhibitor (e.g. temsirolimus) therapy or a neprilysin inhibitor may be at increased risk for angioedema [see Drug Interactions (7.7)].

Intestinal Angioedema

Intestinal angioedema has been reported in patients treated with ACE inhibitors. These patients presented with abdominal pain (with or without nausea or vomiting); in some cases there was no prior history of facial angioedema and C-1 esterase levels were normal. The angioedema was diagnosed by procedures including abdominal CT scan or ultrasound, or at surgery, and symptoms resolved after stopping the ACE inhibitor. Include intestinal angioedema in the differential diagnosis of patients on ACE inhibitors presenting with abdominal pain.

Anaphylactoid Reactions During Desensitization

Two patients undergoing desensitizing treatment with hymenoptera venom while receiving ACE inhibitors sustained life-threatening anaphylactoid reactions. In the same patients, these reactions were avoided when ACE inhibitors were temporarily withheld, but they reappeared upon inadvertent rechallenge.

Anaphylactoid Reactions During Membrane Exposure

Anaphylactoid reactions have been reported in patients dialyzed with high-flux membranes and treated concomitantly with an ACE inhibitor. Anaphylactoid reactions have also been reported in patients undergoing low-density lipoprotein apheresis with dextran sulfate absorption.

5.2 Hepatic Failure and Impaired Liver Function

Rarely, ACE inhibitors, including ALTACE, have been associated with a syndrome that starts with cholestatic jaundice and progresses to fulminant hepatic necrosis and sometimes death. The mechanism of this syndrome is not understood. Discontinue ALTACE if patient develops jaundice or marked elevations of hepatic enzymes.

As ramipril is primarily metabolized by hepatic esterases to its active moiety, ramiprilat, patients with impaired liver function could develop markedly elevated plasma levels of ramipril. No formal pharmacokinetic studies have been carried out in hypertensive patients with impaired liver function.

5.3 Renal Impairment

As a consequence of inhibiting the renin-angiotensin-aldosterone system, changes in renal function may be anticipated in susceptible individuals. In patients with severe congestive heart failure whose renal function may depend on the activity of the renin-angiotensin-aldosterone system, treatment with ACE inhibitors, including ALTACE, may be associated with oliguria or progressive azotemia and rarely with acute renal failure or death.

In hypertensive patients with unilateral or bilateral renal artery stenosis, increases in blood urea nitrogen and serum creatinine may occur. Experience with another ACE inhibitor suggests that these increases would be reversible upon discontinuation of ALTACE and/or diuretic therapy. In such patients, monitor renal function during the first few weeks of therapy. Some hypertensive patients with no apparent pre-existing renal vascular disease have developed increases in blood urea nitrogen and serum creatinine, usually minor and transient, especially when ALTACE has been given concomitantly with a diuretic. This is more likely to occur in patients with pre-existing renal impairment. Dosage reduction of ALTACE and/or discontinuation of the diuretic may be required.

5.4 Neutropenia and Agranulocytosis

In rare instances, treatment with ACE inhibitors may be associated with mild reductions in red blood cell count and hemoglobin content, blood cell or platelet counts. In isolated cases, agranulocytosis, pancytopenia, and bone marrow depression may occur. Hematological reactions to ACE inhibitors are more likely to occur in patients with collagen-vascular disease (e.g., systemic lupus erythematosus, scleroderma) and renal impairment. Consider monitoring white blood cell counts in patients with collagen-vascular disease, especially if the disease is associated with impaired renal function.

5.5 Hypotension

General Considerations

ALTACE can cause symptomatic hypotension, after either the initial dose or a later dose when the dosage has been increased. Like other ACE inhibitors, ALTACE, has been only rarely associated with hypotension in uncomplicated hypertensive patients. Symptomatic hypotension is most likely to occur in patients who have been volume- and/or salt-depleted as a result of prolonged diuretic therapy, dietary salt restriction, dialysis, diarrhea, or vomiting. Correct volume- and salt-depletion before initiating therapy with ALTACE.

If excessive hypotension occurs, place the patient in a supine position and, if necessary, treat with intravenous infusion of physiological saline. ALTACE treatment usually can be continued following restoration of blood pressure and volume.

Heart Failure Post-Myocardial Infarction

In patients with heart failure post-myocardial infarction who are currently being treated with a diuretic, symptomatic hypotension occasionally can occur following the initial dose of ALTACE. If the initial dose of 2.5 mg ALTACE cannot be tolerated, use an initial dose of 1.25 mg ALTACE to avoid excessive hypotension. Consider reducing the dose of concomitant diuretic to decrease the incidence of hypotension.

Congestive Heart Failure

In patients with congestive heart failure, with or without associated renal insufficiency, ACE inhibitor therapy may cause excessive hypotension, which may be associated with oliguria or azotemia and rarely, with acute renal failure and death. In such patients, initiate ALTACE therapy under close medical supervision and follow patients closely for the first 2 weeks of treatment and whenever the dose of ALTACE or diuretic is increased.

Surgery and Anesthesia

In patients undergoing surgery or during anesthesia with agents that produce hypotension, ramipril may block angiotensin II formation that would otherwise occur secondary to compensatory renin release. Hypotension that occurs as a result of this mechanism can be corrected by volume expansion.

5.6 Fetal Toxicity

Use of drugs that act on the renin-angiotensin system during the second and third trimesters of pregnancy reduces fetal renal function and increases fetal and neonatal morbidity and death. Resulting oligohydramnios can be associated with fetal lung hypoplasia and skeletal deformations. Potential neonatal adverse effects include skull hypoplasia, anuria, hypotension, renal failure, and death. When pregnancy is detected, discontinue ALTACE as soon as possible [see Use in Specific Populations (8.1)].

5.7 Dual Blockade of the Renin-Angiotensin System

Dual blockade of the RAS with angiotensin receptor blockers, ACE inhibitors, or aliskiren is associated with increased risks of hypotension, hyperkalemia, and changes in renal function (including acute renal failure) compared to monotherapy. Most patients receiving the combination of two RAS inhibitors do not obtain any additional benefit compared to monotherapy. In general, avoid combined use of RAS inhibitors. Closely monitor blood pressure, renal function and electrolytes in patients on ALTACE and other agents that affect the RAS.

Telmisartan

The ONTARGET trial enrolled 25,620 patients >55 years old with atherosclerotic disease or diabetes with end-organ damage, randomized them to telmisartan only, ramipril only, or the combination, and followed them for a median of 56 months. Patients receiving the combination of telmisartan and ramipril did not obtain any benefit in the composite endpoint of cardiovascular death, MI, stroke and heart failure hospitalization compared to monotherapy, but experienced an increased incidence of clinically important renal dysfunction (death, doubling of serum creatinine, or dialysis) compared with groups receiving telmisartan alone or ramipril alone. Concomitant use of telmisartan and ramipril is not recommended.

Aliskiren

Do not co-administer aliskiren with ALTACE in patients with diabetes. Avoid concomitant use of aliskiren with ALTACE in patients with renal impairment (GFR <60 mL/min/1.73 m^2).

5.8 Hyperkalemia

In clinical trials with ALTACE, hyperkalemia (serum potassium >5.7 mEq/L) occurred in approximately 1% of hypertensive patients receiving ALTACE. In most cases, these were isolated values, which resolved despite continued therapy. None of these patients were discontinued from the trials because of hyperkalemia. Risk factors for the development of hyperkalemia include renal insufficiency, diabetes mellitus, and the concomitant use of other drugs that raise serum potassium levels. Monitor serum potassium in such patients [see Drug Interactions (7.2)].

5.9 Cough

Presumably caused by inhibition of the degradation of endogenous bradykinin, persistent nonproductive cough has been reported with all ACE inhibitors, always resolving after discontinuation of therapy. Consider the possibility of angiotensin converting enzyme inhibitor induced-cough in the differential diagnosis of cough.

6 ADVERSE REACTIONS

6.1 Clinical Trials Experience

Because clinical trials are conducted under widely varying conditions, the adverse reaction rates observed in the clinical trials of a drug cannot be directly compared to rates in the clinical trials of another drug and may not reflect the rates observed in practice.

Hypertension

ALTACE has been evaluated for safety in over 4000 patients with hypertension; of these, 1230 patients were studied in U.S. controlled trials, and 1107 were studied in foreign controlled trials. Almost 700 of these patients were treated for at least one year. The overall incidence of reported adverse events was similar in ALTACE and placebo patients. The most frequent clinical side effects (possibly or probably related to study drug) reported by patients receiving ALTACE in placebo-controlled trials were: headache (5.4%), dizziness (2.2%), and fatigue or asthenia (2.0%), but only the last one was more common in ALTACE patients than in patients given placebo. Generally the side effects were mild and transient, and there was no relation to total dosage within the range of 1.25 mg–20 mg. Discontinuation of therapy because of a side effect was required in approximately 3% of U.S. patients treated with ALTACE. The most common reasons for discontinuation were: cough (1.0%), dizziness (0.5%), and impotence (0.4%).

Of observed side effects considered possibly or probably related to study drug that occurred in U.S. placebo-controlled trials in more than 1% of patients treated with ALTACE, only asthenia (fatigue) was more common on ALTACE than placebo (2% [n=13/651] vs. 1% [n=2/286], respectively).

In placebo-controlled trials, there was also an excess of upper respiratory infection and flu syndrome in the ALTACE group, not attributed at that time to ramipril. As these studies were carried out before the relationship of cough to ACE inhibitors was recognized, some of these events may represent ramipril-induced cough. In a later 1-year study, increased cough was seen in almost 12% of ALTACE patients, with about 4% of patients requiring discontinuation of treatment.

Reduction in the Risk of Myocardial Infarction, Stroke, and Death from Cardiovascular Causes

HOPE Study

Safety data in the Heart Outcomes Prevention Evaluation (HOPE) study were collected as reasons for discontinuation or temporary interruption of treatment. The incidence of cough was similar to that seen in the Acute Infarction Ramipril Efficacy (AIRE) trial. The rate of angioedema was the same as in previous clinical trials [see Warnings and Precautions (5.1)].

Table 1. Reasons for Discontinuation or Temporary Interruption of Treatment—HOPE Study
 | Placebo (N=4652) | ALTACE (N=4645)
Discontinuation at any time | 32% | 34%
Permanent discontinuation | 28% | 29%
Reasons for stopping
Cough | 2% | 7%
Hypotension or dizziness | 1.5% | 1.9%
Angioedema | 0.1% | 0.3%

Heart Failure Post-Myocardial Infarction

AIRE Study

Adverse reactions (except laboratory abnormalities) considered possibly/probably related to study drug that occurred in more than 1% of patients and more frequently on ALTACE are shown below. The incidences are from the AIRE study. The follow-up time was between 6 and 46 months for this study.

Table 2. Percentage of Patients with Adverse Events Possibly/ Probably Related to Study Drug—Placebo-Controlled (AIRE) Mortality Study
Adverse Event | Placebo (N=982) | ALTACE (N=1004)
Hypotension | 5% | 11%
Cough increased | 4% | 8%
Dizziness | 3% | 4%
Angina pectoris | 2% | 3%
Nausea | 1% | 2%
Postural hypotension | 1% | 2%
Syncope | 1% | 2%
Vomiting | 0.5% | 2%
Vertigo | 0.7% | 2%
Abnormal kidney function | 0.5% | 1%
Diarrhea | 0.4% | 1%

Other Adverse Reactions

Other adverse reactions reported in controlled clinical trials (in less than 1% of ALTACE patients), or rarer events seen in post-marketing experience, include the following (in some, a causal relationship to drug is uncertain):

Body as a whole: Anaphylactoid reactions [see Warnings and Precautions (5.1)].

Cardiovascular: Symptomatic hypotension (reported in 0.5% of patients in U.S. trials) [see Warnings and Precautions (5.5)], syncope, and palpitations.

Hematologic: Pancytopenia, hemolytic anemia, and thrombocytopenia.

Decreases in hemoglobin or hematocrit (a low value and a decrease of 5 g/dL or 5%, respectively) were rare, occurring in 0.4% of patients receiving ALTACE alone and in 1.5% of patients receiving ALTACE plus a diuretic.

Renal: Acute renal failure. Some hypertensive patients with no apparent pre-existing renal disease have developed minor, usually transient, increases in blood urea nitrogen and serum creatinine when taking ALTACE, particularly when ALTACE was given concomitantly with a diuretic [see Warnings and Precautions (5.3)].

Angioneurotic edema: Angioneurotic edema has been reported in 0.3% of patients in U.S. clinical trials of ALTACE [see Warnings and Precautions (5.1) ].

Gastrointestinal: Hepatic failure, hepatitis, jaundice, pancreatitis, abdominal pain (sometimes with enzyme changes suggesting pancreatitis), anorexia, constipation, diarrhea, dry mouth, dyspepsia, dysphagia, gastroenteritis, increased salivation, and taste disturbance.

Dermatologic: Apparent hypersensitivity reactions (manifested by urticaria, pruritus, or rash, with or without fever), photosensitivity, purpura, onycholysis, pemphigus, pemphigoid, erythema multiforme, toxic epidermal necrolysis, and Stevens-Johnson syndrome.

Neurologic and Psychiatric: Anxiety, amnesia, convulsions, depression, hearing loss, insomnia, nervousness, neuralgia, neuropathy, paresthesia, somnolence, tinnitus, tremor, vertigo, and vision disturbances.

Miscellaneous: As with other ACE inhibitors, a symptom complex has been reported which may include a positive ANA, an elevated erythrocyte sedimentation rate, arthralgia/arthritis, myalgia, fever, vasculitis, eosinophilia, photosensitivity, rash and other dermatologic manifestations. Additionally, as with other ACE inhibitors, eosinophilic pneumonitis has been reported.

Other: Arthralgia, arthritis, dyspnea, edema, epistaxis, impotence, increased sweating, malaise, myalgia, and weight gain.

6.2 Post-Marketing Experience

In addition to adverse reactions reported from clinical trials, there have been rare reports of hypoglycemia reported during ALTACE therapy when given to patients concomitantly taking oral hypoglycemic agents or insulin. The causal relationship is unknown.

6.3 Clinical Laboratory Test Findings

Creatinine and Blood Urea Nitrogen: Increases in creatinine levels occurred in 1.2% of patients receiving ALTACE alone, and in 1.5% of patients receiving ALTACE and a diuretic. Increases in blood urea nitrogen levels occurred in 0.5% of patients receiving ALTACE alone and in 3% of patients receiving ALTACE with a diuretic. None of these increases required discontinuation of treatment. Increases in these laboratory values are more likely to occur in patients with renal insufficiency or those pretreated with a diuretic and, based on experience with other ACE inhibitors, would be expected to be especially likely in patients with renal artery stenosis [see Warnings and Precautions (5.3)]. As ramipril decreases aldosterone secretion, elevation of serum potassium can occur. Use potassium supplements and potassium sparing diuretics with caution, and monitor the patient's serum potassium frequently [see Warnings and Precautions (5.8)].

Hemoglobin and Hematocrit: Decreases in hemoglobin or hematocrit (a low value and a decrease of 5 g/dL or 5%, respectively) were rare, occurring in 0.4% of patients receiving ALTACE alone and in 1.5% of patients receiving ALTACE plus a diuretic. No US patients discontinued treatment because of decreases in hemoglobin or hematocrit.

Other (causal relationships unknown): Clinically important changes in standard laboratory tests were rarely associated with ALTACE administration. Elevations of liver enzymes, serum bilirubin, uric acid, and blood glucose have been reported, as have cases of hyponatremia and scattered incidents of leucopenia, eosinophilia, and proteinuria. In US trials, less than 0.2% of patients discontinued treatment for laboratory abnormalities; all of these were cases of proteinuria or abnormal liver-function tests.

7 DRUG INTERACTIONS

7.1 Diuretics

Patients on diuretics, especially those in whom diuretic therapy was recently instituted, may occasionally experience an excessive reduction of blood pressure after initiation of therapy with ALTACE. The possibility of hypotensive effects with ALTACE can be minimized by either decreasing or discontinuing the diuretic or increasing the salt intake prior to initiation of treatment with ALTACE. If this is not possible, reduce the starting dose [see Dosage and Administration (2)].

7.2 Agents Increasing Serum Potassium

Coadministration of ALTACE with other drugs that raise serum potassium levels may result in hyperkalemia. Monitor serum potassium in such patients.

7.3 Other Agents Affecting RAS

In general, avoid combined use of RAS inhibitors. [see Warnings and Precautions (5.7)]. Do not co-administer aliskiren with ALTACE in patients with diabetes [see Contraindications (4)].

7.4 Lithium

Increased serum lithium levels and symptoms of lithium toxicity have been reported in patients receiving ACE inhibitors during therapy with lithium; therefore, frequent monitoring of serum lithium levels is recommended. If a diuretic is also used, the risk of lithium toxicity may be increased.

7.5 Gold

Nitritoid reactions (symptoms include facial flushing, nausea, vomiting and hypotension) have been reported rarely in patients on therapy with injectable gold (sodium aurothiomalate) and concomitant ACE inhibitor therapy including ALTACE.

7.6 Non-Steroidal Anti-Inflammatory Agents including Selective Cyclooxygenase-2 Inhibitors (COX-2 Inhibitors)

In patients who are elderly, volume-depleted (including those on diuretic therapy), or with compromised renal function, co-administration of NSAIDs, including selective COX-2 inhibitors, with ACE inhibitors, including ramipril, may result in deterioration of renal function, including possible acute renal failure. These effects are usually reversible. Monitor renal function periodically in patients receiving ramipril and NSAID therapy.

The antihypertensive effect of ACE inhibitors, including ramipril, may be attenuated by NSAIDs.

7.7 mTOR Inhibitors or Other Drugs Known to Cause Angioedema

Patients taking concomitant mTOR inhibitor (e.g. temsirolimus) therapy or a neprilysin inhibitor may be at increased risk for angioedema [see Warnings and Precautions (5.1)].

8 USE IN SPECIFIC POPULATIONS

8.1 Pregnancy

Use of drugs that act on the renin-angiotensin system during the second and third trimesters of pregnancy reduces fetal renal function and increases fetal and neonatal morbidity and death. Resulting oligohydramnios can be associated with fetal lung hypoplasia and skeletal deformations. Potential neonatal adverse effects include skull hypoplasia, anuria, hypotension, renal failure, and death. When pregnancy is detected, discontinue ALTACE as soon as possible. These adverse outcomes are usually associated with use of these drugs in the second and third trimester of pregnancy. Most epidemiologic studies examining fetal abnormalities after exposure to antihypertensive use in the first trimester have not distinguished drugs affecting the renin-angiotensin system from other antihypertensive agents. Appropriate management of maternal hypertension during pregnancy is important to optimize outcomes for both mother and fetus.

In the unusual case that there is no appropriate alternative to therapy with drugs affecting the renin-angiotensin system for a particular patient, apprise the mother of the potential risk to the fetus. Perform serial ultrasound examinations to assess the intra-amniotic environment. If oligohydramnios is observed, discontinue ALTACE unless it is considered life-saving for the mother. Fetal testing may be appropriate, based on the week of pregnancy. Patients and physicians should be aware, however, that oligohydramnios may not appear until after the fetus has sustained irreversible injury. Closely observe infants with histories of in utero exposure to ALTACE for hypotension, oliguria, and hyperkalemia [see Use in Specific Populations (8.4)].

8.3 Nursing Mothers

Ingestion of a single 10 mg oral dose of ALTACE resulted in undetectable amounts of ramipril and its metabolites in breast milk. However, because multiple doses may produce low milk concentrations that are not predictable from a single dose, do not use ALTACE in nursing mothers.

8.4 Pediatric Use

Neonates with a history of in utero exposure to ALTACE:

If oliguria or hypotension occurs, direct attention toward support of blood pressure and renal perfusion. Exchange transfusions or dialysis may be required as a means of reversing hypotension and/or substituting for disordered renal function. Ramipril, which crosses the placenta, can be removed from the neonatal circulation by these means, but limited experience has not shown that such removal is central to the treatment of these infants.

Safety and effectiveness in pediatric patients have not been established. Irreversible kidney damage has been observed in very young rats given a single dose of ALTACE.

8.5 Geriatric Use

Of the total number of patients who received ALTACE in U.S. clinical studies of ALTACE, 11.0% were ≥65 years of age while 0.2% were ≥75 years of age. No overall differences in effectiveness or safety were observed between these patients and younger patients, and other reported clinical experience has not identified differences in responses between the elderly and younger patients, but a greater sensitivity of some older individuals cannot be ruled out.

One pharmacokinetic study conducted in hospitalized elderly patients indicated that peak ramiprilat levels and area under the plasma concentration-time curve (AUC) for ramiprilat are higher in older patients.

8.6 Renal Impairment

A single-dose pharmacokinetic study was conducted in hypertensive patients with varying degrees of renal impairment who received a single 10 mg dose of ramipril. Patients were stratified into four groups based on initial estimates of creatinine clearance: normal (>80 mL/min), mild impairment (40–80 mL/min), moderate impairment (15–40 mL/min), and severe impairment (<15 mL/min). On average, the AUC0–24h for ramiprilat was approximately 1.7-fold higher, 3.0-fold higher, and 3.2-fold higher in the groups with mild, moderate, and severe renal impairment, respectively, compared to the group with normal renal function. Overall, the results suggest that the starting dose of ramipril should be adjusted downward in patients with moderate-to-severe renal impairment.

10 OVERDOSAGE

Single oral doses of ramipril in rats and mice of 10 g/kg–11 g/kg resulted in significant lethality. In dogs, oral doses as high as 1 g/kg induced only mild gastrointestinal distress. Limited data on human overdosage are available. The most likely clinical manifestations would be symptoms attributable to hypotension.

Laboratory determinations of serum levels of ramipril and its metabolites are not widely available, and such determinations have, in any event, no established role in the management of ramipril overdose.

No data are available to suggest physiological maneuvers (e.g., maneuvers to change the pH of the urine) that might accelerate elimination of ramipril and its metabolites. Similarly, it is not known which, if any, of these substances can be effectively removed from the body by hemodialysis.

Angiotensin II could presumably serve as a specific antagonist-antidote in the setting of ramipril overdose, but angiotensin II is essentially unavailable outside of scattered research facilities. Because the hypotensive effect of ramipril is achieved through vasodilation and effective hypovolemia, it is reasonable to treat ramipril overdose by infusion of normal saline solution.

11 DESCRIPTION

Ramipril is a 2-aza-bicyclo [3.3.0]-octane-3-carboxylic acid derivative. It is a white, crystalline substance soluble in polar organic solvents and buffered aqueous solutions. Ramipril melts between 105°–112°C.

The CAS Registry Number is 87333-19-5. Ramipril's chemical name is (2S,3aS,6aS)-1[(S)-N-[(S)-1-Carboxy-3-phenylpropyl] alanyl] octahydrocyclopenta [b]pyrrole-2-carboxylic acid, 1-ethyl ester.

The inactive ingredients present are pregelatinized starch NF, gelatin, and titanium dioxide. The 1.25 mg capsule shell contains yellow iron oxide, the 2.5 mg capsule shell contains D&C yellow #10 and FD&C red #40, the 5 mg capsule shell contains FD&C blue #1 and FD&C red #40, and the 10 mg capsule shell contains FD&C blue #1.

The structural formula for ramipril is:

Its empirical formula is C23H32N2O5 and its molecular weight is 416.5.

Ramiprilat, the diacid metabolite of ramipril, is a non-sulfhydryl ACE inhibitor. Ramipril is converted to ramiprilat by hepatic cleavage of the ester group.

12 CLINICAL PHARMACOLOGY

12.1 Mechanism of Action

Ramipril and ramiprilat inhibit ACE in human subjects and animals. Angiotensin converting enzyme is a peptidyl dipeptidase that catalyzes the conversion of angiotensin I to the vasoconstrictor substance, angiotensin II. Angiotensin II also stimulates aldosterone secretion by the adrenal cortex. Inhibition of ACE results in decreased plasma angiotensin II, which leads to decreased vasopressor activity and to decreased aldosterone secretion. The latter decrease may result in a small increase of serum potassium. In hypertensive patients with normal renal function treated with ALTACE alone for up to 56 weeks, approximately 4% of patients during the trial had an abnormally high serum potassium and an increase from baseline greater than 0.75 mEq/L, and none of the patients had an abnormally low potassium and a decrease from baseline greater than 0.75 mEq/L. In the same study, approximately 2% of patients treated with ALTACE and hydrochlorothiazide for up to 56 weeks had abnormally high potassium values and an increase from baseline of 0.75 mEq/L or greater; and approximately 2% had abnormally low values and decreases from baseline of 0.75 mEq/L or greater [see Warnings and Precautions (5.8)]. Removal of angiotensin II negative feedback on renin secretion leads to increased plasma renin activity.

The effect of ramipril on hypertension appears to result at least in part from inhibition of both tissue and circulating ACE activity, thereby reducing angiotensin II formation in tissue and plasma.

Angiotensin converting enzyme is identical to kininase, an enzyme that degrades bradykinin. Whether increased levels of bradykinin, a potent vasopressor peptide, play a role in the therapeutic effects of ALTACE remains to be elucidated.

While the mechanism through which ALTACE lowers blood pressure is believed to be primarily suppression of the renin-angiotensin-aldosterone system, ALTACE has an antihypertensive effect even in patients with low-renin hypertension. Although ALTACE was antihypertensive in all races studied, Black hypertensive patients (usually a low-renin hypertensive population) had a blood pressure lowering response to monotherapy, albeit a smaller average response, than non-Black patients.

12.2 Pharmacodynamics

Single doses of ramipril of 2.5 mg–20 mg produce approximately 60%–80% inhibition of ACE activity 4 hours after dosing with approximately 40%–60% inhibition after 24 hours. Multiple oral doses of ramipril of 2.0 mg or more cause plasma ACE activity to fall by more than 90% 4 hours after dosing, with over 80% inhibition of ACE activity remaining 24 hours after dosing. The more prolonged effect of even small multiple doses presumably reflects saturation of ACE binding sites by ramiprilat and relatively slow release from those sites.

12.3 Pharmacokinetics

Absorption

Following oral administration of ALTACE, peak plasma concentrations (Cmax) of ramipril are reached within 1 hour. The extent of absorption is at least 50%–60%, and is not significantly influenced by the presence of food in the gastrointestinal tract, although the rate of absorption is reduced.

In a trial in which subjects received ALTACE capsules or the contents of identical capsules dissolved in water, dissolved in apple juice, or suspended in applesauce, serum ramiprilat levels were essentially unrelated to the use or non-use of the concomitant liquid or food.

Distribution

Cleavage of the ester group (primarily in the liver) converts ramipril to its active diacid metabolite, ramiprilat. Peak plasma concentrations of ramiprilat are reached 2–4 hours after drug intake. The serum protein binding of ramipril is about 73% and that of ramiprilat about 56%; in vitro, these percentages are independent of concentration over the range of 0.01 µg/mL–10 µg/mL.

Metabolism

Ramipril is almost completely metabolized to ramiprilat, which has about 6 times the ACE inhibitory activity of ramipril, and to the diketopiperazine ester, the diketopiperazine acid, and the glucuronides of ramipril and ramiprilat, all of which are inactive.

Plasma concentrations of ramipril and ramiprilat increase with increased dose, but are not strictly dose-proportional. The 24-hour AUC for ramiprilat, however, is dose-proportional over the 2.5 mg–20 mg dose range. The absolute bioavailabilities of ramipril and ramiprilat were 28% and 44%, respectively, when 5 mg of oral ramipril was compared with the same dose of ramipril given intravenously.

After once-daily dosing, steady-state plasma concentrations of ramiprilat are reached by the fourth dose. Steady-state concentrations of ramiprilat are somewhat higher than those seen after the first dose of ALTACE, especially at low doses (2.5 mg), but the difference is clinically insignificant.

Plasma concentrations of ramiprilat decline in a triphasic manner (initial rapid decline, apparent elimination phase, terminal elimination phase). The initial rapid decline, which represents distribution of the drug into a large peripheral compartment and subsequent binding to both plasma and tissue ACE, has a half-life of 2–4 hours. Because of its potent binding to ACE and slow dissociation from the enzyme, ramiprilat shows two elimination phases. The apparent elimination phase corresponds to the clearance of free ramiprilat and has a half-life of 9–18 hours. The terminal elimination phase has a prolonged half-life (>50 hours) and probably represents the binding/dissociation kinetics of the ramiprilat/ACE complex. It does not contribute to the accumulation of the drug. After multiple daily doses of ALTACE 5 mg–10 mg, the half-life of ramiprilat concentrations within the therapeutic range was 13–17 hours.

In patients with creatinine clearance <40 mL/min/1.73 m^2, peak levels of ramiprilat are approximately doubled, and trough levels may be as much as quintupled. In multiple-dose regimens, the total exposure to ramiprilat (AUC) in these patients is 3–4 times as large as it is in patients with normal renal function who receive similar doses.

In patients with impaired liver function, the metabolism of ramipril to ramiprilat appears to be slowed, possibly because of diminished activity of hepatic esterases, and plasma ramipril levels in these patients are increased about 3-fold. Peak concentrations of ramiprilat in these patients, however, are not different from those seen in subjects with normal hepatic function, and the effect of a given dose on plasma ACE activity does not vary with hepatic function.

Excretion

After oral administration of ramipril, about 60% of the parent drug and its metabolites are eliminated in the urine, and about 40% is found in the feces. Drug recovered in the feces may represent both biliary excretion of metabolites and/or unabsorbed drug, however the proportion of a dose eliminated by the bile has not been determined. Less than 2% of the administered dose is recovered in urine as unchanged ramipril.

The urinary excretion of ramipril, ramiprilat, and their metabolites is reduced in patients with impaired renal function. Compared to normal subjects, patients with creatinine clearance <40 mL/min/1.73 m^2 had higher peak and trough ramiprilat levels and slightly longer times to peak concentrations.

13 NONCLINICAL TOXICOLOGY

13.1 Carcinogenesis, Mutagenesis, Impairment of Fertility

No evidence of a tumorigenic effect was found when ramipril was given by gavage to rats for up to 24 months at doses of up to 500 mg/kg/day or to mice for up to 18 months at doses of up to 1000 mg/kg/day. (For either species, these doses are about 200 times the maximum recommended human dose when compared on the basis of body surface area.) No mutagenic activity was detected in the Ames test in bacteria, the micronucleus test in mice, unscheduled DNA synthesis in a human cell line, or a forward gene-mutation assay in a Chinese hamster ovary cell line. Several metabolites and degradation products of ramipril were also negative in the Ames test. A study in rats with dosages as great as 500 mg/kg/day did not produce adverse effects on fertility.

No teratogenic effects of ramipril were seen in studies of pregnant rats, rabbits, and cynomolgus monkeys. On a body surface area basis, the doses used were up to approximately 400 times (in rats and monkeys) and 2 times (in rabbits) the recommended human dose.

14 CLINICAL STUDIES

14.1 Hypertension

ALTACE has been compared with other ACE inhibitors, beta-blockers, and thiazide diuretics as monotherapy for hypertension. It was approximately as effective as other ACE inhibitors and as atenolol.

Administration of ALTACE to patients with mild to moderate hypertension results in a reduction of both supine and standing blood pressure to about the same extent with no compensatory tachycardia. Symptomatic postural hypotension is infrequent, although it can occur in patients who are salt- and/or volume-depleted [see Warnings and Precautions (5.5)]. Use of ALTACE in combination with thiazide diuretics gives a blood pressure lowering effect greater than that seen with either agent alone.

In single-dose studies, doses of 5 mg–20 mg of ALTACE lowered blood pressure within 1–2 hours, with peak reductions achieved 3–6 hours after dosing. The antihypertensive effect of a single dose persisted for 24 hours. In longer term (4–12 weeks) controlled studies, once-daily doses of 2.5 mg–10 mg were similar in their effect, lowering supine or standing systolic and diastolic blood pressures 24 hours after dosing by about 6/4 mmHg more than placebo. In comparisons of peak vs. trough effect, the trough effect represented about 50–60% of the peak response. In a titration study comparing divided (bid) vs. qd treatment, the divided regimen was superior, indicating that for some patients, the antihypertensive effect with once-daily dosing is not adequately maintained.

In most trials, the antihypertensive effect of ALTACE increased during the first several weeks of repeated measurements. The antihypertensive effect of ALTACE has been shown to continue during long-term therapy for at least 2 years. Abrupt withdrawal of ALTACE has not resulted in a rapid increase in blood pressure. ALTACE has been compared with other ACE inhibitors, beta-blockers, and thiazide diuretics. ALTACE was approximately as effective as other ACE inhibitors and as atenolol. In both Caucasians and Blacks, hydrochlorothiazide (25 or 50 mg) was significantly more effective than ramipril.

ALTACE was less effective in blacks than in Caucasians. The effectiveness of ALTACE was not influenced by age, sex, or weight.

In a baseline controlled study of 10 patients with mild essential hypertension, blood pressure reduction was accompanied by a 15% increase in renal blood flow. In healthy volunteers, glomerular filtration rate was unchanged.

14.2 Reduction in Risk of Myocardial Infarction, Stroke, and Death from Cardiovascular Causes

The HOPE study was a large, multicenter, randomized, double-blind, placebo-controlled, 2 × 2 factorial design study conducted in 9541 patients (4645 on ALTACE) who were 55 years or older and considered at high risk of developing a major cardiovascular event because of a history of coronary artery disease, stroke, peripheral vascular disease, or diabetes that was accompanied by at least one other cardiovascular risk factor (hypertension, elevated total cholesterol levels, low HDL levels, cigarette smoking, or documented microalbuminuria). Patients were either normotensive or under treatment with other antihypertensive agents. Patients were excluded if they had clinical heart failure or were known to have a low ejection fraction (<0.40). This study was designed to examine the long-term (mean of 5 years) effects of ALTACE (10 mg orally once daily) on the combined endpoint of myocardial infarction, stroke, or death from cardiovascular causes.

The HOPE study results showed that ALTACE (10 mg/day) significantly reduced the rate of myocardial infarction, stroke, or death from cardiovascular causes (826/4652 vs. 651/4645, relative risk 0.78), as well as the rates of the 3 components of the combined endpoint. The relative risk of the composite outcomes in the ALTACE group as compared to the placebo group was 0.78% (95% confidence interval, 0.70–0.86). The effect was evident after about 1 year of treatment.

Table 3. Summary of Combined Components and Endpoints—HOPE Study
Outcome | Placebo (N=4652) n (%) | ALTACE (N=4645) n (%) | Relative Risk (95% CI) P-Value
Combined Endpoint
Myocardial infarction, stroke, or death from cardiovascular cause | 826 (17.8%) | 651 (14.0%) | 0.78 (0.70–0.86) P=0.0001
Component Endpoint
Death from cardiovascular causes | 377 (8.1%) | 282 (6.1%) | 0.74 (0.64–0.87) P=0.0002
Myocardial infarction | 570 (12.3%) | 459 (9.9%) | 0.80 (0.70–0.90) P=0.0003
Stroke | 226 (4.9%) | 156 (3.4%) | 0.68 (0.56–0.84) P=0.0002
Overall Mortality
Death from any cause | 569 (12.2%) | 482 (10.4%) | 0.84 (0.75–0.95) P=0.005

Figure 1. Kaplan-Meier Estimates of the Composite Outcome of Myocardial Infarction, Stroke, or Death from Cardiovascular Causes in the Ramipril Group and the Placebo Group

ALTACE was effective in different demographic subgroups (i.e., gender, age), subgroups defined by underlying disease (e.g., cardiovascular disease, hypertension), and subgroups defined by concomitant medication. There were insufficient data to determine whether or not ALTACE was equally effective in ethnic subgroups.

This study was designed with a prespecified substudy in diabetics with at least one other cardiovascular risk factor. Effects of ALTACE on the combined endpoint and its components were similar in diabetics (N=3577) to those in the overall study population.

Table 4. Summary of Combined Endpoints and Components in Diabetics—HOPE Study
Outcome | Placebo (N=1769) n (%) | ALTACE (N=1808) n (%) | Relative Risk Reduction (95% CI) P-Value
Combined Endpoint
Myocardial infarction, stroke, or death from cardiovascular cause | 351 (19.8%) | 277 (15.3%) | 0.25 (0.12–0.36) P=0.0004
Component Endpoint
Death from cardiovascular causes | 172 (9.7%) | 112 (6.2%) | 0.37 (0.21–0.51) P=0.0001
Myocardial infarction | 229 (12.9%) | 185 (10.2%) | 0.22 (0.06–0.36) P=0.01
Stroke | 108 (6.1%) | 76 (4.2%) | 0.33 (0.10–0.50) P=0.007

Figure 2. The Beneficial Effect of Treatment with ALTACE on the Composite Outcome of Myocardial Infarction, Stroke, or Death from Cardiovascular Causes Overall and in Various Subgroups

Cerebrovascular disease was defined as stroke or transient ischemic attacks. The size of each symbol is proportional to the number of patients in each group. The dashed line indicates overall relative risk.

The benefits of ALTACE were observed among patients who were taking aspirin or other anti-platelet agents, beta-blockers, and lipid-lowering agents as well as diuretics and calcium channel blockers.

14.3 Heart Failure Post-Myocardial Infarction

ALTACE was studied in the AIRE trial. This was a multinational (mainly European) 161-center, 2006-patient, double-blind, randomized, parallel-group study comparing ALTACE to placebo in stable patients, 2–9 days after an acute myocardial infarction, who had shown clinical signs of congestive heart failure at any time after the myocardial infarction. Patients in severe (NYHA class IV) heart failure, patients with unstable angina, patients with heart failure of congenital or valvular etiology, and patients with contraindications to ACE inhibitors were all excluded. The majority of patients had received thrombolytic therapy at the time of the index infarction, and the average time between infarction and initiation of treatment was 5 days.

Patients randomized to ALTACE treatment were given an initial dose of 2.5 mg twice daily. If the initial regimen caused undue hypotension, the dose was reduced to 1.25 mg, but in either event doses were titrated upward (as tolerated) to a target regimen (achieved in 77% of patients randomized to ALTACE) of 5 mg twice daily. Patients were then followed for an average of 15 months, with the range of follow-up between 6 and 46 months.

The use of ALTACE was associated with a 27% reduction (p=0.002) in the risk of death from any cause; about 90% of the deaths that occurred were cardiovascular, mainly sudden death. The risks of progression to severe heart failure and of congestive heart failure-related hospitalization were also reduced, by 23% (p=0.017) and 26% (p=0.011), respectively. The benefits of ALTACE therapy were seen in both genders, and they were not affected by the exact timing of the initiation of therapy, but older patients may have had a greater benefit than those under 65. The benefits were seen in patients on (and not on) various concomitant medications. At the time of randomization these included aspirin (about 80% of patients), diuretics (about 60%), organic nitrates (about 55%), beta-blockers (about 20%), calcium channel blockers (about 15%), and digoxin (about 12%).

16 HOW SUPPLIED/STORAGE AND HANDLING

ALTACE is available in 1.25 mg, 2.5 mg, 5 mg, and 10 mg hard gelatin capsules. Descriptions of ALTACE capsules are summarized below.

Capsule Strength | Capsule Color | Package Configuration | NDC#
1.25 mg | yellow | Bottle of 100 | 61570-110-01
2.5 mg | orange | Bottle of 100 | 61570-111-01
5 mg | red | Bottle of 100 | 61570-112-01
10 mg | Process Blue | Bottle of 100 | 61570-120-01

STORAGE AND HANDLING

Dispense in well-closed container with safety closure.

Store at controlled room temperature (59°–86°F).

17 PATIENT COUNSELING INFORMATION

Angioedema

Angioedema, including laryngeal edema, can occur with treatment with ACE inhibitors, especially following the first dose. Advise patients to immediately report any signs or symptoms suggesting angioedema (swelling of face, eyes, lips, or tongue, or difficulty in breathing) and to temporarily discontinue drug until they have consulted with the prescribing physician.

Neutropenia

Advise patients to promptly report any indication of infection (e.g., sore throat, fever), which could be a sign of neutropenia.

Symptomatic Hypotension

Inform patients that light-headedness can occur, especially during the first days of therapy, and it should be reported. Advise patients to discontinue ALTACE if syncope (fainting) occurs, and to follow up with their health care providers.

Inform patients that inadequate fluid intake or excessive perspiration, diarrhea, or vomiting while taking ALTACE can lead to an excessive fall in blood pressure, with the same consequences of lightheadedness and possible syncope.

Pregnancy

Tell female patients of childbearing age about the consequences of exposure to Altace during pregnancy. Discuss treatment options with women planning to become pregnant. Ask patients to report pregnancies to their physicians as soon as possible.

Hyperkalemia

Advise patients not to use salt substitutes containing potassium without consulting their physician.

LAB-0581-9.0

PRINCIPAL DISPLAY PANEL - 1.25 mg Capsule Bottle Label

NDC 61570-110-01

Pfizer

Altace®
(ramipril) capsules, for oral use

1.25 mg

100 Capsules
Rx only

PRINCIPAL DISPLAY PANEL - 2.5 mg Capsule Bottle Label

NDC 61570-111-01

Pfizer

Altace®
(ramipril) capsules, for oral use

2.5 mg

100 Capsules
Rx only

PRINCIPAL DISPLAY PANEL - 5 mg Capsule Bottle Label

NDC 61570-112-01

Pfizer

Altace®
(ramipril) capsules, for oral use

5 mg

100 Capsules
Rx only

PRINCIPAL DISPLAY PANEL - 10 mg Capsule Bottle Label

NDC 61570-120-01

Pfizer

Altace®
(ramipril) capsules, for oral use

10 mg

100 Capsules
Rx only